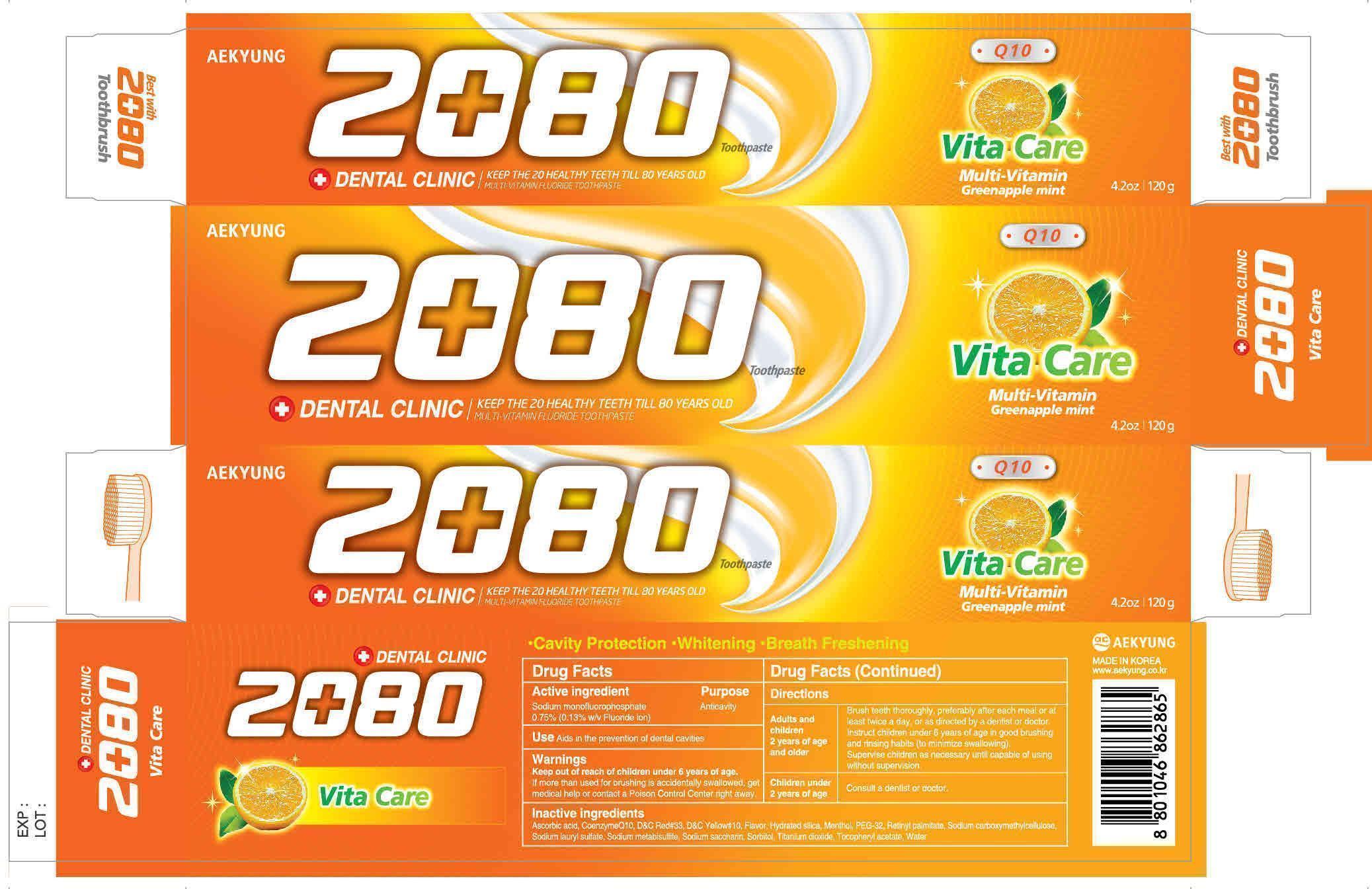 DRUG LABEL: Dental Clinic 2080 Vita Care
NDC: 67225-0004 | Form: PASTE
Manufacturer: Aekyung Industrial Co., Ltd.
Category: otc | Type: HUMAN OTC DRUG LABEL
Date: 20160714

ACTIVE INGREDIENTS: SODIUM MONOFLUOROPHOSPHATE 0.156 g/120 g
INACTIVE INGREDIENTS: SORBITOL 72 g/120 g; SODIUM LAURYL SULFATE 2.64 g/120 g; CARBOXYMETHYLCELLULOSE SODIUM 0.48 g/120 g; TITANIUM DIOXIDE 0.3 g/120 g; SACCHARIN SODIUM 0.12 g/120 g; ALPHA-TOCOPHEROL ACETATE 0.3 g/120 g; HYDRATED SILICA 22.92 g/120 g; WATER 12.81 g/120 g; MENTHOL 0.3 g/120 g

WARNINGS

If more than used for brushing is accidentally swallowed, get medical help or contact a Poison Control Center right away

Keep out of reach of children under 6 years of age

ACTIVE INGREDIENT

Sodium monofluorophosphate 0.75% (0.13% w/v Fluoride ion)

INACTIVE INGREDIENT

Sodium carboxymethylcellulose, Sodium lauryl sulfate, Sodium saccharin, Sorbitol, Titanium dioxide, Tocopheryl acetate, water, Ascorbic acid, Hydrated Silica, Menthol, PEG-32, Sodium metabisullite, Coenzyme Q10, Flavor, Retinyl palmitate, D&C Yellow#10

Purpose Anticavity

DOSAGE AND ADMINISTRATION

Adults and children 2 years of age and older

Brush teeth thoroughly, preferably after each meal or at least twice a day or as directed by a dentist or doctor.

Instruct children under 6 years of age in good brushing ad rinsing habits (to minimize swallowing).

Supervise children as necessary until capable of using without supervision.

Children under 2 years of age

Consult a dentist or doctor

INDICATIONS AND USAGE

Aids in the prevention of dental cavities